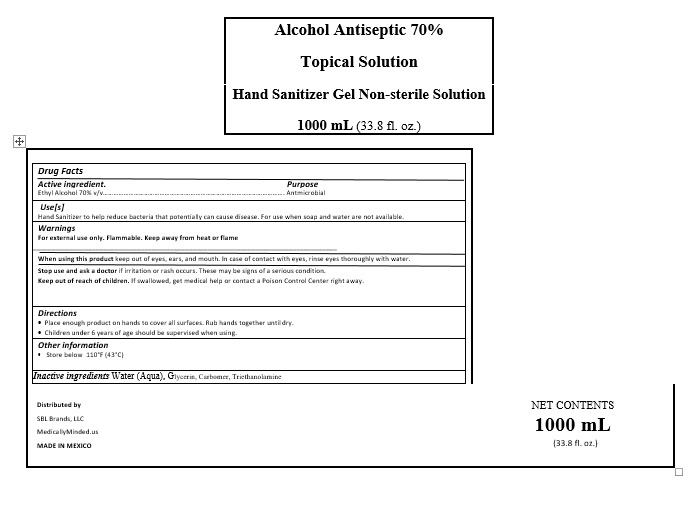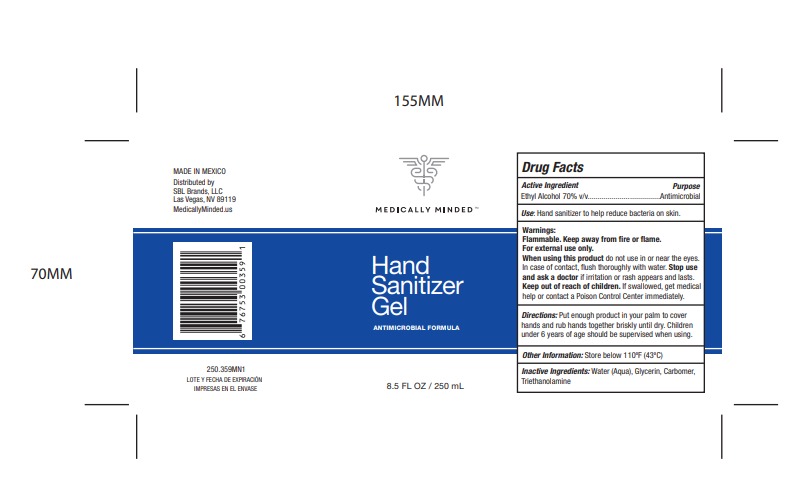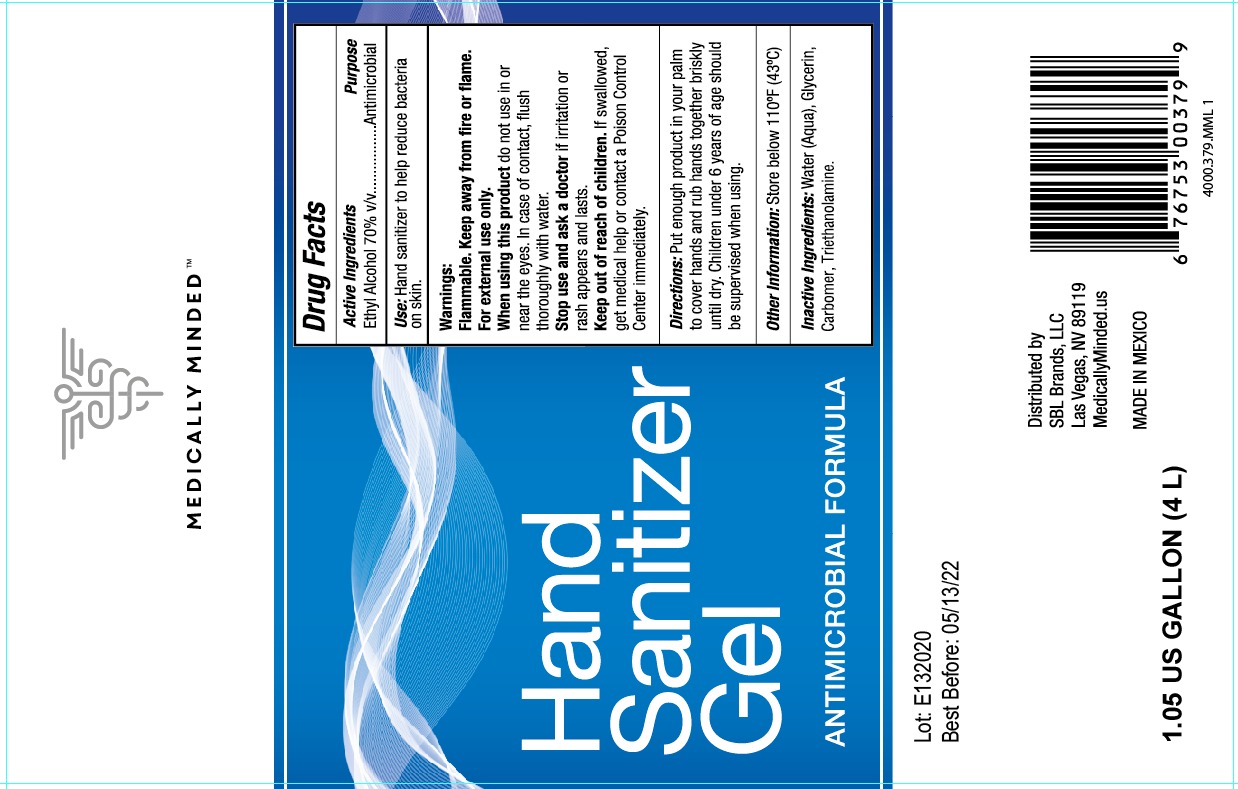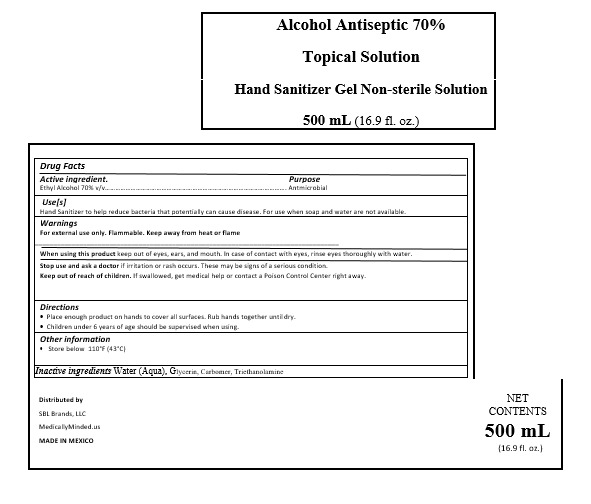 DRUG LABEL: HAND SANITIZER
NDC: 78767-4001 | Form: GEL
Manufacturer: SOLARNA, S.A. DE C.V.
Category: otc | Type: HUMAN OTC DRUG LABEL
Date: 20200605

ACTIVE INGREDIENTS: ALCOHOL 0.7 mL/1 mL
INACTIVE INGREDIENTS: TRIETHANOLAMINE CAPROYL GLUTAMATE 0.002 mL/1 mL; GLYCERIN 0.0375 mL/1 mL; CARBOMER 940 0.002 mL/1 mL; WATER 0.2585 mL/1 mL

HAND SANITIZER GEL

DIRECTIONS AND USAGE

Directions

Place enough product on hands to cover all surfaces. Rub hands together until dry

Use[s]

Hand Sanitizer to help reduce bacteria that potentially can cause disease. For use when soap and water are not available.

INACTIVE INGREDIENTS

Inactive ingredients Water (Aqua), Glycerin, Carbomer, Triethanolamine

Keep out of reach of children. If swallowed, get medical help or contact a Poison Control Center right away.

PURPOSE

Purpose Antmicrobial

WARNINGS AND PRECAUTIONS

Children under 6 years of age should be supervised when using.

Store below 110°F (43°C)

WARNINGS

For external use only. Flammable. Keep away from heat or flame

ACTIVE INGREDIENT

Active ingredient. Ethyl Alcohol 70% v/v

DOSAGE AND ADMINISTRATION

Place enough product on hands to cover all surfaces. Rub hands together until dry

When using this product keep out of eyes, ears, and mouth. In case of contact with eyes, rinse eyes thoroughly with water.

Use[s]

Hand Sanitizer to help reduce bacteria that potentially can cause disease. For use when soap and water are not available.